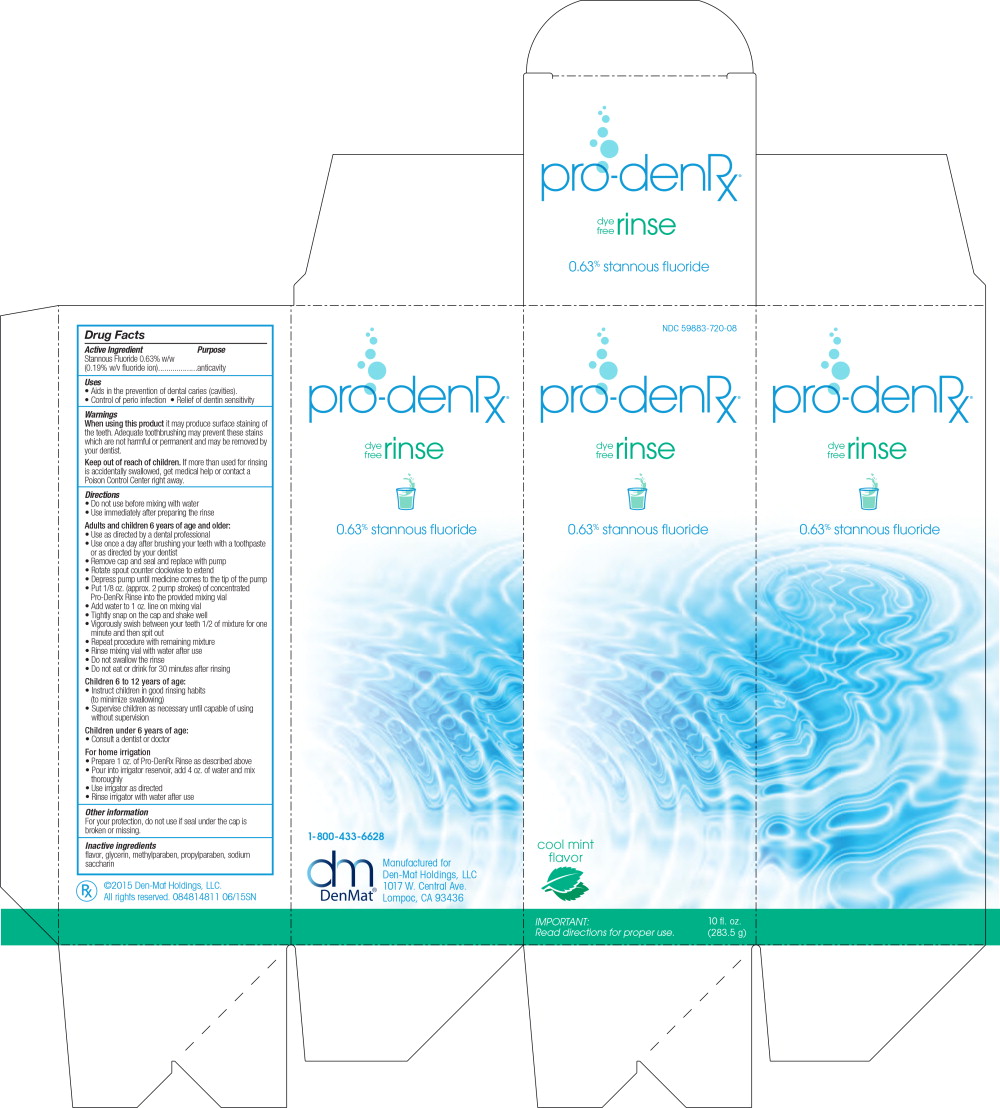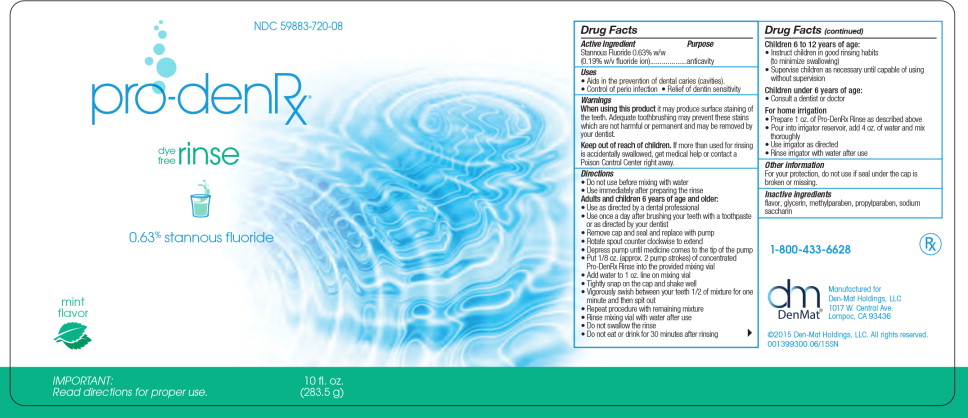 DRUG LABEL: Pro-Den Rx
NDC: 59883-720 | Form: RINSE
Manufacturer: Den-mat Holdings, Llc
Category: otc | Type: HUMAN OTC DRUG LABEL
Date: 20231120

ACTIVE INGREDIENTS: STANNOUS FLUORIDE 1.53 mg/1 g
INACTIVE INGREDIENTS: GLYCERIN; METHYLPARABEN; PROPYLPARABEN; SACCHARIN SODIUM

ProDenRx

Drug Facts

Active Ingredient

Stannous Fluoride 0.63% w/w

(0.19% w/v fluoride ion)

Purpose

anticavity

Uses

- Aids in the prevention of dental caries (cavities).
- Control of perio infection
- Relief of dentin sensitivity

Warnings

When using this product it may produce surface staining of the teeth. Adequate toothbrushing may prevent these stains which are not harmful or permanent and may be removed by your dentist.

Keep out of reach of children. If more than used for rinsing s accidentally swallowed, get medical help or contact a Poison Control Center right away.

Directions

- Do not use before mixing with water
- Use immediately after preparing the rinse

Adults and children 6 years of age and older:

- Use as directed by a dental professional
- Use once a day after brushing your teeth with a toothpaste or as directed by your dentist
- Remove cap and seal and replace with pump
- Rotate spout counter clockwise to extend
- Depress pump until medicine comes to the tip of the pump
- Put 1/8 oz. (approx. 2 pump strokes) of concentrated Pro-DenRx Rinse into the provided mixing vial
- Add water to 1 oz. line on mixing vial
- Tightly snap on the cap and shake well
- Vigorously swish between your teeth 1/2 of mixture for one minute and then spit out
- Repeat procedure with remaining mixture
- Rinse mixing vial with water after use
- Do not swallow the rinse
- Do not eat or drink for 30 minutes after rinsing

Children 6 to 12 years of age:

- Instruct children in good rinsing habits (to minimize swallowing)
- Supervise children as necessary until capable of using without supervision

Children under 6 years of age:

- Consult a dentist or doctor For home irrigation
- Prepare 1 oz. of Pro-DenRx Rinse as described above
- Pour into irrigator reservoir, add 4 oz. of water and mix thoroughly
- Use irrigator as directed
- Rinse irrigator with water after use

Other information

For your protection, do not use if seal under the cap is broken or missing.

Inactive ingredients

flavor, glycerin, methylparaben, propylparaben, sodium saccharin

Principal Display Panel - Carton Label

NDC 59883-720-08

pro-denRx®

dye
free
rinse

0.63% stannous fluoride

cool mint
flavor

IMPORTANT:

Read directions for proper use.

10 fl. oz.
(283.5 g)

Principal Display Panel

NDC 59883-720-08

pro-denRx®

dye
free
rinse

0.63% stannous fluoride

mint
flavor

IMPORTANT:

Read directions for proper use.

10 fl. oz.
(283.5 g)